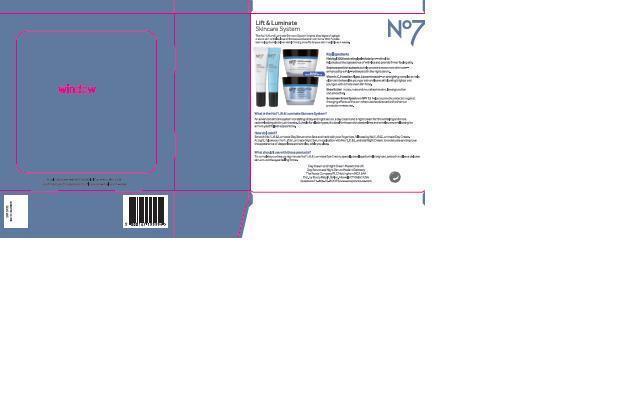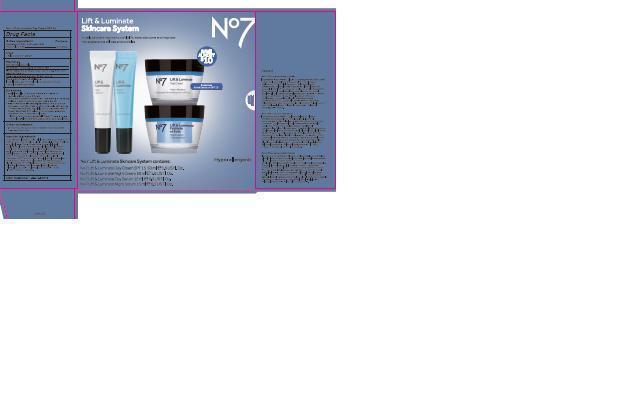 DRUG LABEL: No7  Lift and Luminite Day Cream SPF 15
NDC: 11489-087 | Form: CREAM
Manufacturer: BCM Ltd
Category: otc | Type: HUMAN OTC DRUG LABEL
Date: 20140915

ACTIVE INGREDIENTS: AVOBENZONE 1.5 g/50 g; OCTINOXATE 2.5 g/50 g; OCTOCRYLENE 0.5 g/50 g
INACTIVE INGREDIENTS: WATER; GLYCERIN; C12-15 ALKYL BENZOATE; SHEA BUTTER; BUTYLENE GLYCOL; CETEARYL GLUCOSIDE; DIMETHICONE; MICA; CETOSTEARYL ALCOHOL; CYCLOMETHICONE 5; AMMONIUM ACRYLOYLDIMETHYLTAURATE/VP COPOLYMER; PHENOXYETHANOL; CYCLOMETHICONE 6; DIPALMITOYL HYDROXYPROLINE; POTASSIUM CETYL PHOSPHATE; XANTHAN GUM; METHYLPARABEN; SODIUM ASCORBYL PHOSPHATE; DIMETHICONOL (100000 CST); ETHYLPARABEN; DIPROPYLENE GLYCOL; EDETATE SODIUM; TERT-BUTYL ALCOHOL; CITRIC ACID MONOHYDRATE; LUPINUS ALBUS SEED; CARBOMER 940; POLYSORBATE 20; HAEMATOCOCCUS PLUVIALIS; BUTYLATED HYDROXYTOLUENE; POTASSIUM SORBATE; BUTYLPARABEN; PROPYLPARABEN; ISOBUTYLPARABEN; PALMITOYL OLIGOPEPTIDE; PALMITOYL TETRAPEPTIDE-7; BIOTIN; TITANIUM DIOXIDE

No7 Lift and Luminate Day Cream SPF 15

Carton Active Ingredients Section

Active ingredients

Avobenzone 3%

Octinoxate 6%

Octocrylene 1%

Uses

Uses - helps prevent sunburn

Warnings

For external use only

Do not use on damaged or broken skin

When using this product keep out of eyes. Rinse with water to remove.

Ask a doctor

Stop use and ask a doctor if rash occurs

Keep out of reach of children

If swallowed, get medical help or contact a Poison Control Center right away

Directions

Apply liberally 15 minutes before sun exposure

reapply at least every 2 hours

use a water resistnat sunscreen if swimming or sweating

children under 6 months of age: Ask a doctor

Sun Protection Measures. Spending time in the sun increases your risk of skin cancer and early skin aging.

To decrease this risk, regularly use a sunscreen with a Broad Spectrum SPF value of 15 or higher and other sun protection measures including:

Limit time in the sun, especially from 10 a.m - 2 p.m.

wear long-sleeved shirts,pants,hats and sunglasses.

Storage

Other information

Protect the product in this container from excessive heat and direct sun

Inactive ingredients

Aqua(Water), Glycerin, C12-15 alkyl benzoate, Butyrospermum parkii(Shea) butter, butylene glycol, cetearyl glucoside, C18-36 acid glycol ester, Dimethicone, Mica, Cetearyl alcohol, Cyclopentasiloxane, Ammonium acryloydimethyltaurate/VP copolymer, Phenoxyethanol, Cyclohexasiloxane, Potassium cetyl phosphate, Dipalmitoyl hydroxyproline, Xanthan gum, Methylparaben, Sodium ascorbyl phosphate, Dimethiconol, Parfum(fragrance), Ethylparaben, Dipropylene glycol, Tetrasodium EDTA, Citric acid, T-buytl alcohol, Lupinus albus seed extract, Carbomer, Polysorbate-20, Haeamatococcus pluvialis powder, BHT, Polyglucuronic acid, Potassium sorbate, Silica, Butylparaben, Propylparaben, Isobutylparaben, Palmitoyl tripeptide-1, Palmitoyl tetrapeptide-7, Biotin, CI 77891 (Titanium dioxide)

PATIENT COUNSELING INFORMATION

Made in the UK

The Boots Company PLC Nottingham England NG2 3AA

Dist. by Boots Retail USA Inc. Norwalk CT 06851 USA

www.boots.com

DESCRIPTION

Lift and Luminate Skincare System

The No7 Lift and Luminate Skincare System targets 3 key signs of aging in mature skin: wrinkles, loss of firmness and uneven skin tone. With Peptide technology to help deliver visible firming benefitss to your skin in as little as 4 weeks.

Key Ingredients

Matrixyl 3000 and Retinyl palmitate (Pro-retinol) to help reduce the appearance of wrinkles and provide firmer feeling skin.

Sophora and Kiwi extracts to help provide a more even skin tone - enhanced by a Poly-hydroxyacid in the night serum.

Vitamin C, Hawaiian algae, Lipoaminoacid - an energising complex to help older skin behave like younger skin and leave skin looking brighter and younger, with a more even skin tone.

Shea butter moisturizes and noursihes the skin leaving it softer and smoother

Sunscreen Broad Spectrum SPF 15 helps to provide protection against the aging effects of the sun when used as directed with other sun protection measures.

What is the No7 Lift and Luminate Skincare System?

An advanced skincare system consisting of day and night serum, a day cream and a night cream for firmer feeling and more radiant-looking skin in just 4 weeks. Suitable for all skin types, it is ideal for those with deeper lines and wrinkles who are looking for a more youthful appearance.

How do I use it?

Smooth No7 Lift and Luminate Day Serum onto face and neck with your finger tips, followed by No7 Lift and Luminate Day Cream. At night, follow your No7 Lift and Luminate Night Serum application with No7 Lift and Luminate Night Cream, to moisturise and improve the appearance of deeper lines and wrinkles while you sleep.

What should I use with these products?

To complete your beauty regime use No7 Lift and Luminate Eye Cream, specially developed to help brighten, smooth and leave delicate skin around the eyes feeling firmer.